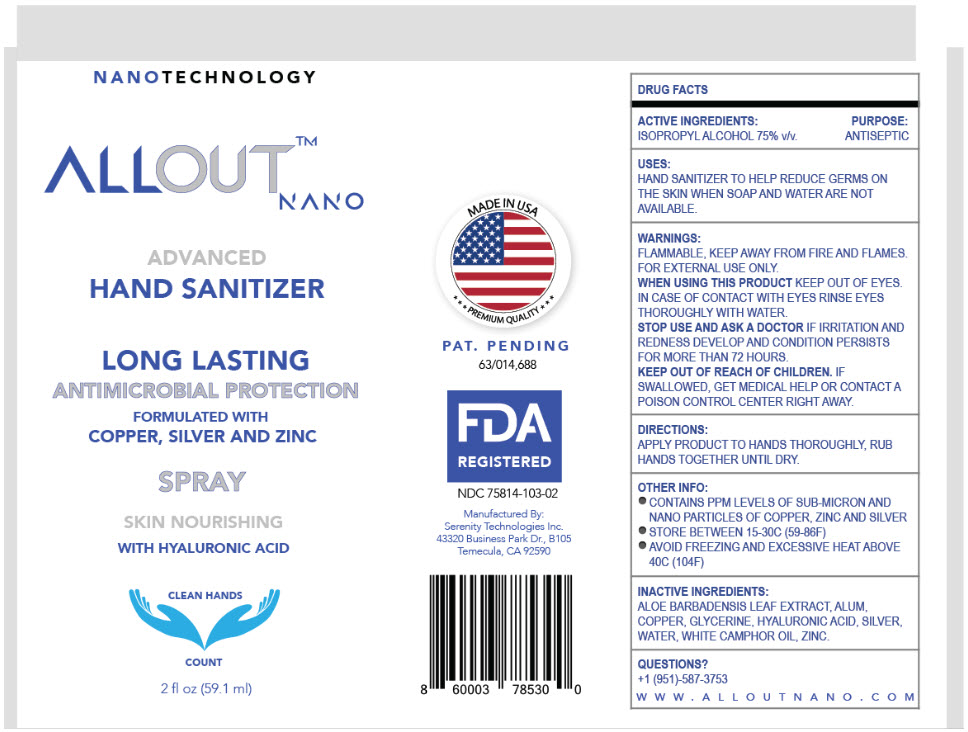 DRUG LABEL: ALLOUT NANO
NDC: 75814-103 | Form: SPRAY
Manufacturer: SERENITY TECHNOLOGIES INC.
Category: otc | Type: HUMAN OTC DRUG LABEL
Date: 20200810

ACTIVE INGREDIENTS: ISOPROPYL ALCOHOL 75 mL/100 mL
INACTIVE INGREDIENTS: POTASSIUM ALUM; SILVER; COPPER; PYRITHIONE ZINC; CAMPHOR OIL, WHITE; HYALURONIC ACID; ALOE VERA LEAF; GLYCERIN

ALLOUT™ NANO

DRUG FACTS

ACTIVE INGREDIENTS

ISOPROPYL ALCOHOL 75% v/v.

PURPOSE

ANTISEPTIC

USES

HAND SANITIZER TO HELP REDUCE GERMS ON THE SKIN WHEN SOAP AND WATER ARE NOT AVAILABLE.

WARNINGS

FLAMMABLE, KEEP AWAY FROM FIRE AND FLAMES. FOR EXTERNAL USE ONLY.

WHEN USING THIS PRODUCT KEEP OUT OF EYES. IN CASE OF CONTACT WITH EYES RINSE EYES THOROUGHLY WITH WATER.

STOP USE AND ASK A DOCTOR IF IRRITATION AND REDNESS DEVELOP AND CONDITION PERSISTS FOR MORE THAN 72 HOURS.

KEEP OUT OF REACH OF CHILDREN. IF SWALLOWED, GET MEDICAL HELP OR CONTACT A POISON CONTROL CENTER RIGHT AWAY.

DIRECTIONS

APPLY PRODUCT TO HANDS THOROUGHLY, RUB HANDS TOGETHER UNTIL DRY.

OTHER INFO

- CONTAINS PPM LEVELS OF SUB-MICRON AND NANO PARTICLES OF COPPER, ZINC AND SILVER
- STORE BETWEEN 15-30C (59-86F)
- AVOID FREEZING AND EXCESSIVE HEAT ABOVE 40C (104F)

INACTIVE INGREDIENTS

ALOE BARBADENSIS LEAF EXTRACT, ALUM, COPPER, GLYCERINE, HYALURONIC ACID, SILVER, WATER, WHITE CAMPHOR OIL, ZINC.

QUESTIONS?

+1 (951)-587-3753

WWW.ALLOUTNANO.COM

Manufactured By:
Serenity Technologies Inc.
43320 Business Park Dr., B105
Temecula, CA 92590

PRINCIPAL DISPLAY PANEL - 59.1 ml Bottle Label

NANOTECHNOLOGY

ALLOUT™
NANO

ADVANCED
HAND SANITIZER

LONG LASTING
ANTIMICROBIAL PROTECTION
FORMULATED WITH
COPPER, SILVER AND ZINC

SPRAY

SKIN NOURISHING
WITH HYALURONIC ACID

CLEAN HANDS

COUNT

2 fl oz (59.1 ml)